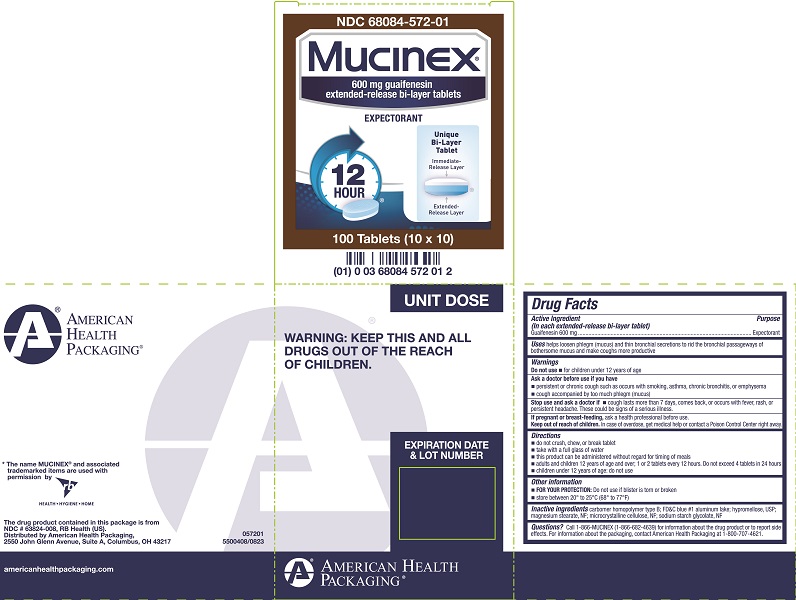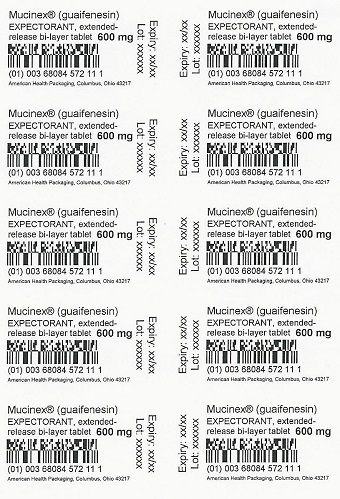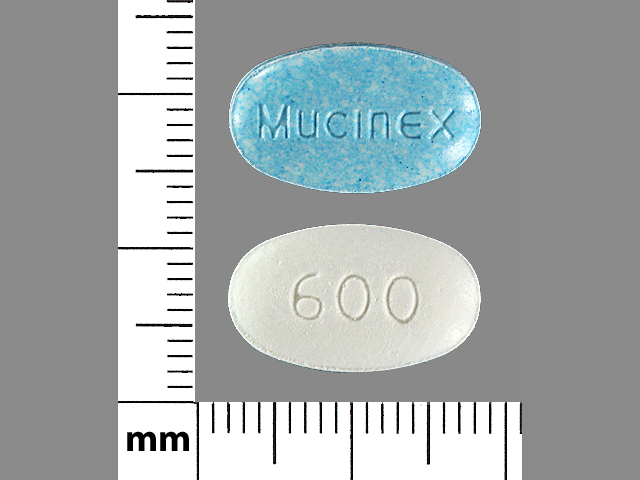 DRUG LABEL: Mucinex
NDC: 68084-572 | Form: TABLET, EXTENDED RELEASE
Manufacturer: American Health Packaging
Category: otc | Type: HUMAN OTC DRUG LABEL
Date: 20240725

ACTIVE INGREDIENTS: GUAIFENESIN 600 mg/1 1
INACTIVE INGREDIENTS: FD&C BLUE NO. 1; ALUMINUM OXIDE; HYPROMELLOSES; MAGNESIUM STEARATE; CELLULOSE, MICROCRYSTALLINE; CARBOMER HOMOPOLYMER TYPE B (ALLYL PENTAERYTHRITOL CROSSLINKED)

Mucinex®

Drug Facts

Active ingredient (in each extended-release bi-layer tablet)

Guaifenesin 600 mg

Purpose

Expectorant

Uses

helps loosen phlegm (mucus) and thin bronchial secretions to rid the bronchial passageways of bothersome mucus and make coughs more productive

Warnings

Do not use

- for children under 12 years of age

Ask a doctor before use if you have

- persistent or chronic cough such as occurs with smoking, asthma, chronic bronchitis, or emphysema
- cough accompanied by too much phlegm (mucus)

Stop use and ask a doctor if

- cough lasts more than 7 days, comes back, or occurs with fever, rash, or persistent headache. These could be signs of a serious illness.

PREGNANCY OR BREAST FEEDING

If pregnant or breast-feeding, ask a health professional before use.

Keep out of reach of children. In case of overdose, get medical help or contact a Poison Control Center right away.

Directions

- do not crush, chew, or break tablet
- take with a full glass of water
- this product can be administered without regard for the timing of meals
- adults and children 12 years of age and over: 1 or 2 tablets every 12 hours. Do not exceed 4 tablets in 24 hours.
- children under 12 years of age: do not use

Other information

- FOR YOUR PROTECTION: Do not use if blister is torn or broken.
- store between 20-25°C (68-77°F)

Inactive ingredients

carbomer homopolymer type B; FD&C blue #1 aluminum lake; hypromellose, USP; magnesium stearate, NF; microcrystalline cellulose, NF; sodium starch glycolate, NF

Questions?

1-866-MUCINEX (1-866-682-4639) for information about the drug product or to report side effects. For information about packaging, contact American Health Packaging at 1-800-707-4621.

*The name MUCINEX® and associated trademarked items are used with permission by Reckitt Benckiser

The drug product contained in this package is from NDC # 63824-008 Reckitt Benckiser.

Packaged and Distributed by American Health Packaging, 2550 John Glenn Avenue, Suite A, Columbus, OH 43217

057201
5500408/0915

Principal Display Panel – Carton – 600 mg

NDC 68084-572-01

Mucinex®

600 mg guaifenesin
extended-release bi-layer tablets

EXPECTORANT

100 Tablets (10 x 10)

Principal Display Panel – Blister – 600 mg

Mucinex® (guaifenesin)
EXPECTORANT extended-
release bi-layer tablet 600 mg